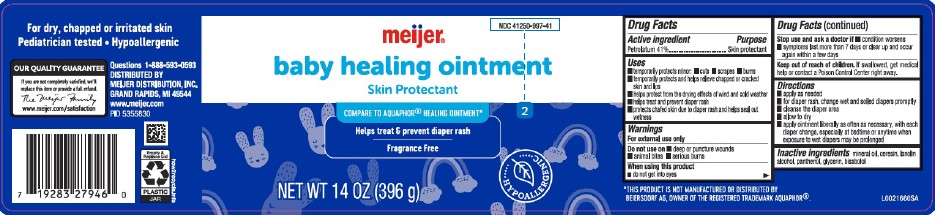 DRUG LABEL: Healing for Babies
NDC: 41250-997 | Form: OINTMENT
Manufacturer: Meijer, Inc.
Category: otc | Type: HUMAN OTC DRUG LABEL
Date: 20260219

ACTIVE INGREDIENTS: PETROLATUM 410 mg/1 g
INACTIVE INGREDIENTS: MINERAL OIL; CERESIN; LANOLIN ALCOHOLS; PANTHENOL; GLYCERIN; LEVOMENOL

Meijer 180.000/180AA-AC
Healing Ointment for Babies

Active ingredient

Petrolatum 41%

Purpose

Skin protectant

Uses

- temporarily protects minor: cuts, scrapes, burns
- temporarily protects and helps relieve chapped or cracked skin and lips
- helps protect from the drying effects of wind and cold weather
- helps treat and prevent diaper rash
- protects chafed skin due to diaper rash and helps seal out wetness

Warnings

For external use only

Do not use on

- deep or puncture wounds
- animal bites
- serious burns

When using this product

- do not get into eyes

Stop use and ask a doctor if

- condition worsens
- symptoms last more than 7 days or clear up and occur again within a few days

Keep out of reach of children.

If swallowed, get medical help or contact a Poison Control Center right away.

Directions

- apply as needed
- for diaper rash, change wet and soiled diapers promptly
- cleanse the diaper area
- allow to dry
- apply ointment liberally as often as necessary, with each diaper change, especially at bedtime or anytime when exposure to wet diapers may be prolonged

Inactive ingredients

mineral oil, ceresin, lanolin alcohol, panthenol, glycerin, bisabolol

Disclaimer

*This product is not manufactured or distributed by Beiersdorf, AG., owner of the registered trademark Aquaphor®.

Claims

For dry, chapped or irritated skin

Pediatrician tested

Hypoallergenic

Adverse Reaction

OUR QUALITY GUARANTEE

If you are not completely satisfied, we'll replace this item or provide a full refund.

The Meijer Family

www.meijer.com/satisfaction

Questions 1-888-593-0593

DISTRIBUTED BY

MEIJER DISTRIBUTION, INC.

GRAND RAPIDS, MI 49544

www.meijer.com

Empty & Replace Lid

PLASTIC JAR

how2recycle.info

PRINCIPAL DISPLAY PANEL

NDC 41250-997-41

meijer®

baby healing ointment

Skin Protectant

COMPARE TO AQUAPHOR® HEALING OINTMENT*

helps treat & prevent diaper rash

Fragrance Free

HYPOALLERGENIC

NET WT 14 OZ (396 g)